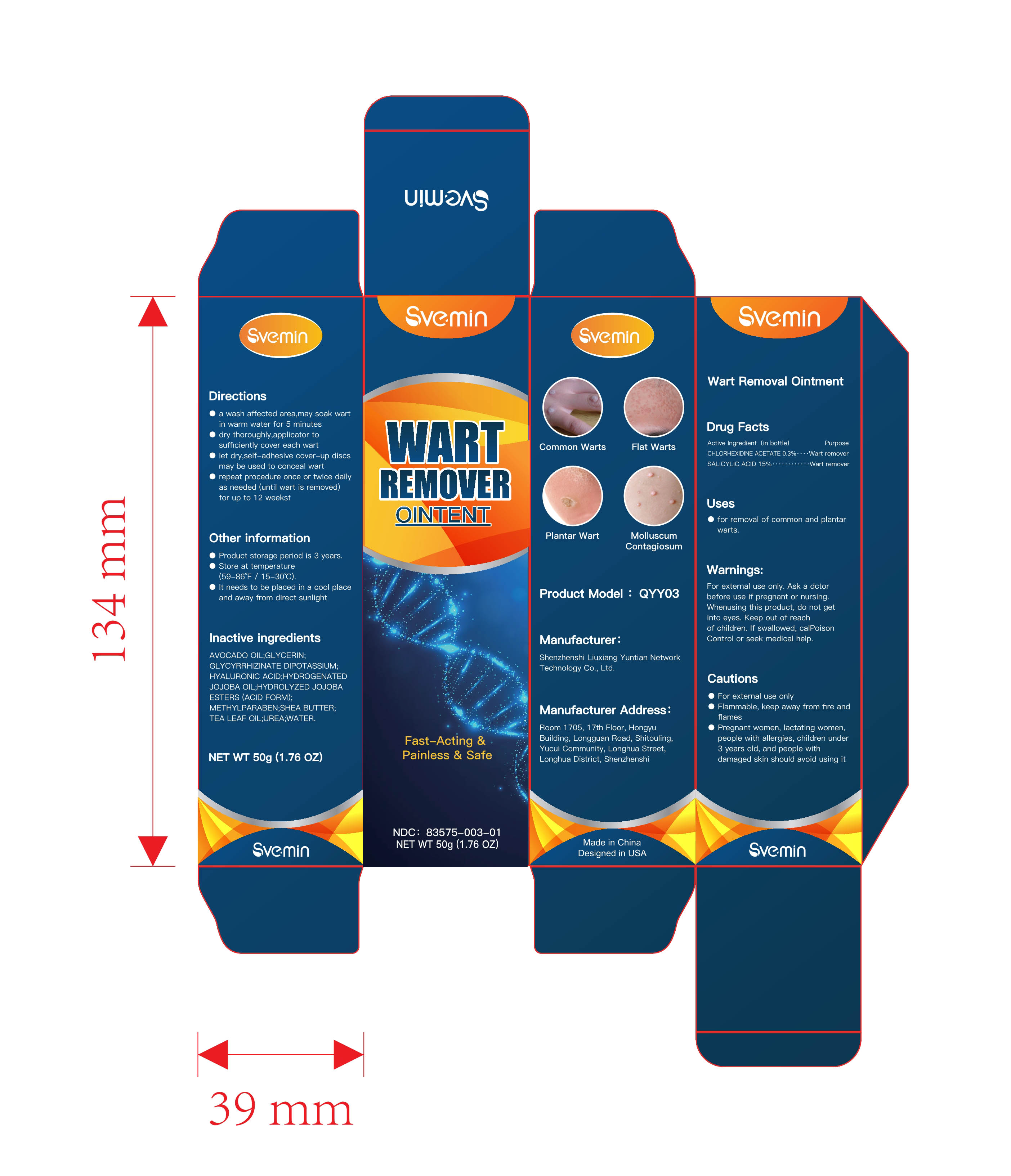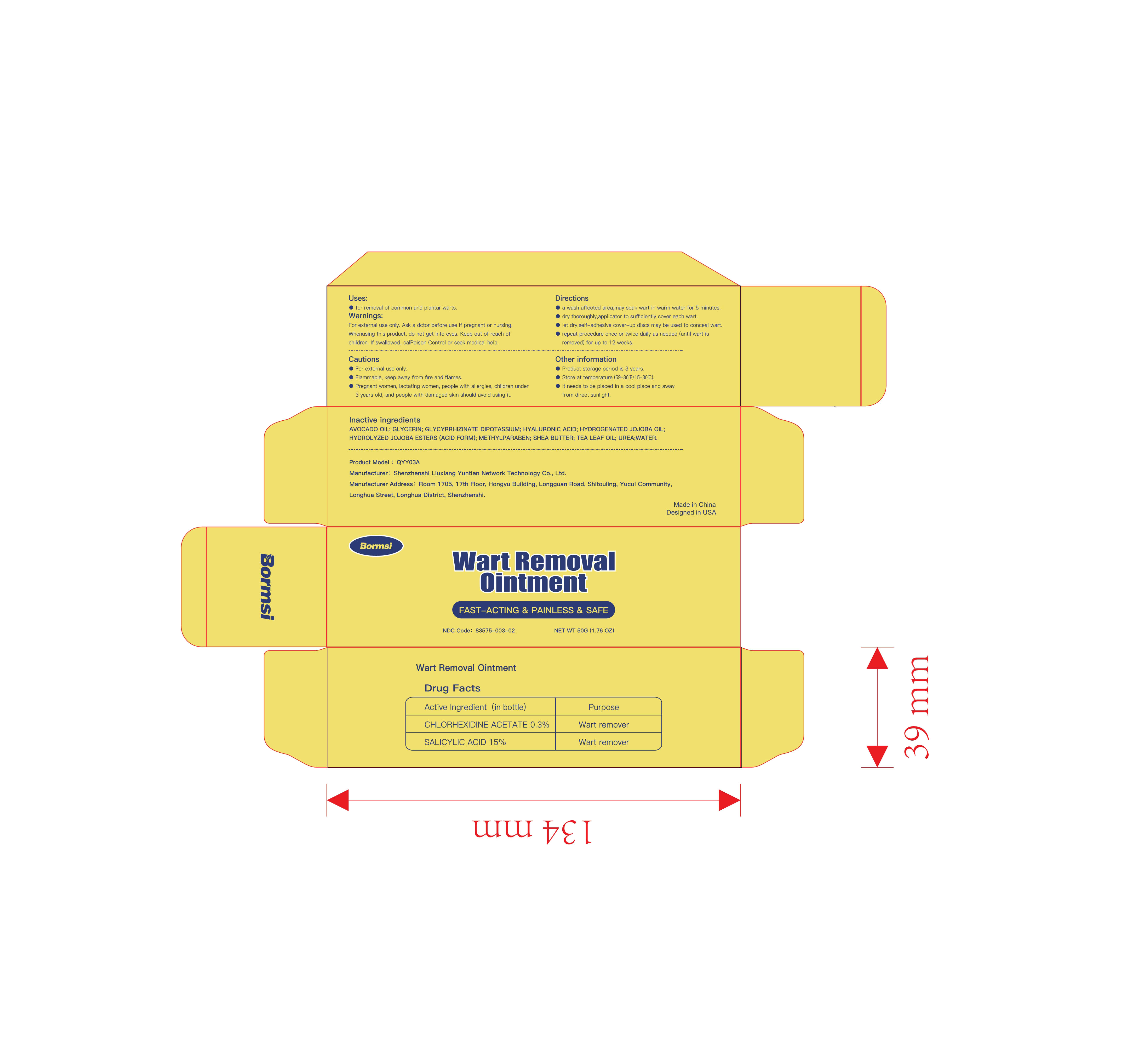 DRUG LABEL: Wart Removal
NDC: 83575-003 | Form: OINTMENT
Manufacturer: Shenzhenshi Liuxiang Yuntian Network Technology Co., Ltd.
Category: otc | Type: HUMAN OTC DRUG LABEL
Date: 20231029

ACTIVE INGREDIENTS: SALICYLIC ACID 15 g/100 g; CHLORHEXIDINE ACETATE 0.3 g/100 g
INACTIVE INGREDIENTS: SHEA BUTTER; HYDROLYZED JOJOBA ESTERS (ACID FORM); UREA; HYALURONIC ACID; WATER; GLYCERIN; AVOCADO OIL; GLYCYRRHIZINATE DIPOTASSIUM; HYDROGENATED JOJOBA OIL; METHYLPARABEN; TEA LEAF OIL

83575-003

ACTIVE INGREDIENT

SALICYLIC ACID 15%

CHLORHEXIDINE ACETATE 0.3%

Purpose

Wart remover

Uses

- For removal of common and plantar warts.

Warnings

For external use only. Ask a actorbefore use if pregnant or nursing. Whenusing this product , do not get into eyes. Keep out of reachof children . If swallowed, calpoison Control or seek medical help.

DO NOT USE

Cautions
- For external use only
- Flammable, keep away from fire and flames
- Pregnant women, lactating women, people with allergies, children under 3 years old, and people with damaged skin should avoid using it

When using this product

Keep out of reach of children. If swallowed by mistake, get medical help or contact a Poison Control Center right away.

STOP USE

If swallowed . calpoisonControl or seek medical help

Keep out of reach of children.

Directions

- a wash affected area , may soak wart in warmwater for 5 minuteso

- dry thoroughly, apply one drop at a time withapplicator to sufficiently cover each wart

- let dry , self-adhesive cover-up discs may beused to conceal wart
- Repeat procedure once or twice daily as needed (until wart is removed) for up to 12 weeks

Other information

- Product storage period is 3 years

- Store at temperature (59-86℉ / 15-30℃).
- It needs to be placed in a cool place and awayfrom direct sunlight

INACTIVE INGREDIENT

AVOCADO OIL, GLYCERIN, GLYCYRRHIZINATE DIPOTASSIUM, HYALURONIC ACID, HYDROGENATED JOJOBA OIL, HYDROLYZED JOJOBA ESTERS (ACID FORM), METHYLPARABEN, SHEA BUTTER, TEA LEAF OIL, UREA, WATER